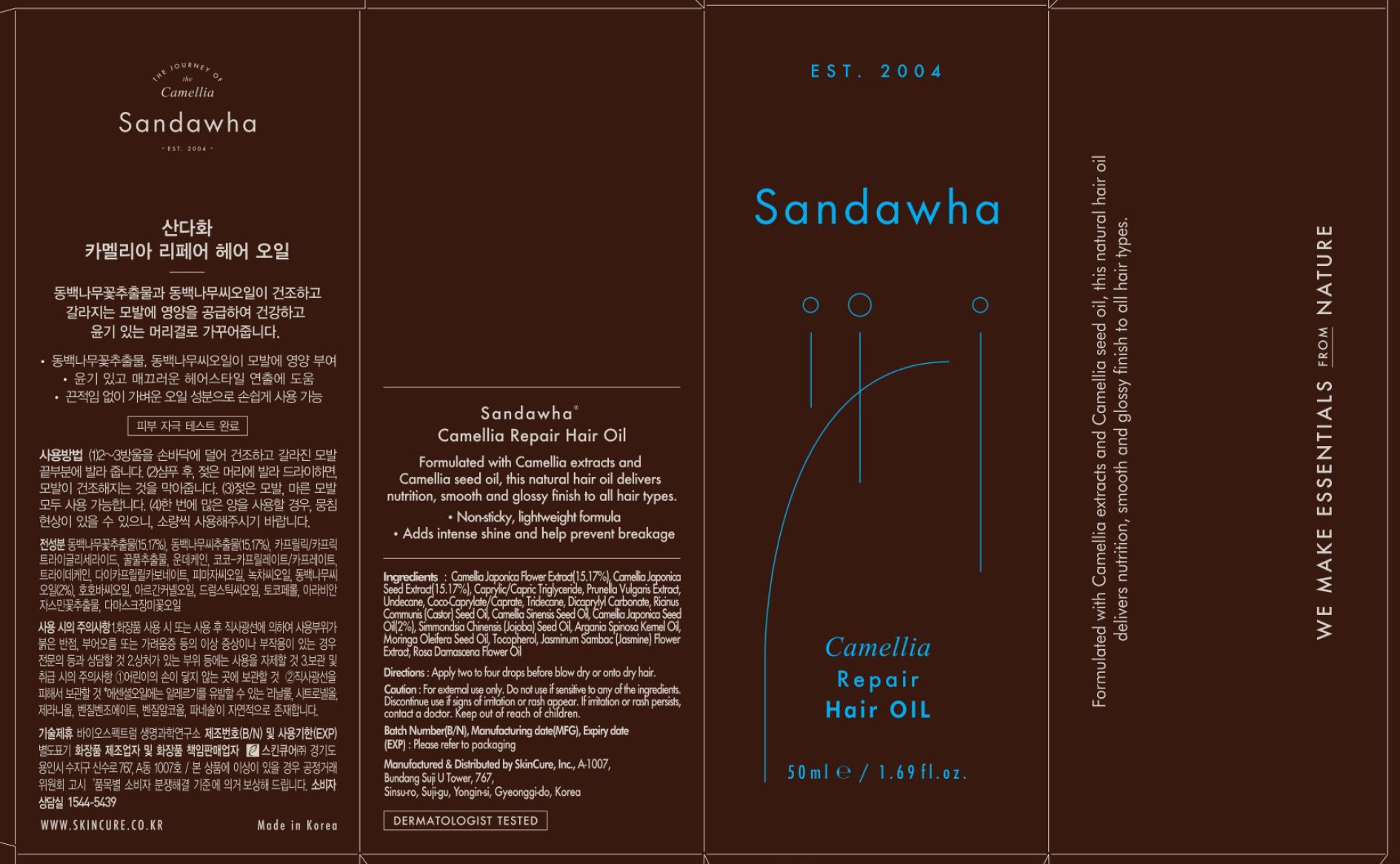 DRUG LABEL: Sandawha Camellia Repair Hair Oil
NDC: 72289-0011 | Form: LIQUID
Manufacturer: SKINCURE INC
Category: otc | Type: HUMAN OTC DRUG LABEL
Date: 20201124

ACTIVE INGREDIENTS: CAMELLIA JAPONICA SEED OIL 2 g/100 mL
INACTIVE INGREDIENTS: TRIDECANE; DICAPRYLYL CARBONATE; UNDECANE

Drug Facts

ACTIVE INGREDIENT

Camellia Japonica Seed Oil

INACTIVE INGREDIENT

DongbakEx
Camellia Japonica Flower Extract 43.3300
Camellia Japonica Seed Extract
Caprylic/Capric Triglyceride
Camellia Sinensis Seed Oil
Hypoil
Prunella Vulgaris Extract 30.0000
Coco-Caprylate/Caprate
Dicaprylyl Carbonate
Caprylic/Capric Triglyceride
Simmondsia chinensis (Jojoba) Seed Oil
Argania Spinosa Kernel Oil
Moringa Oleifera Seed Oil
Cetiol Ultimate
Undecane 15.0000
Tridecane
Ricinus Communis (Castor) Seed Oil 5.0000
Camellia Sinensis Seed Oil 4.0000
Tocopherol 0.5000
Jasminum Sambac (Jasmine) Flower Extract 0.1200
Rosa Damascena Flower Oil 0.0500

PURPOSE

repair hair oil

keep out of reach of the children

INDICATIONS AND USAGE

apply two to four drops before blow dry or onto dry hair

WARNINGS

for external use only

do not use if sensitive to any of the ingredients

discontinue use if signs of irritation or rash appear

if irritation or rash persists, contact a doctor

DOSAGE AND ADMINISTRATION

for external use only